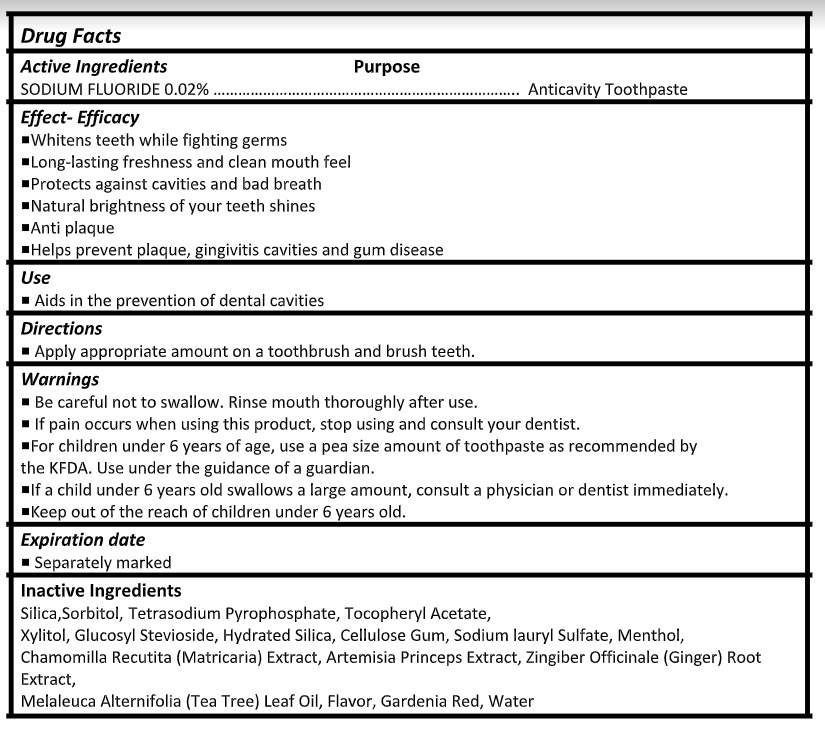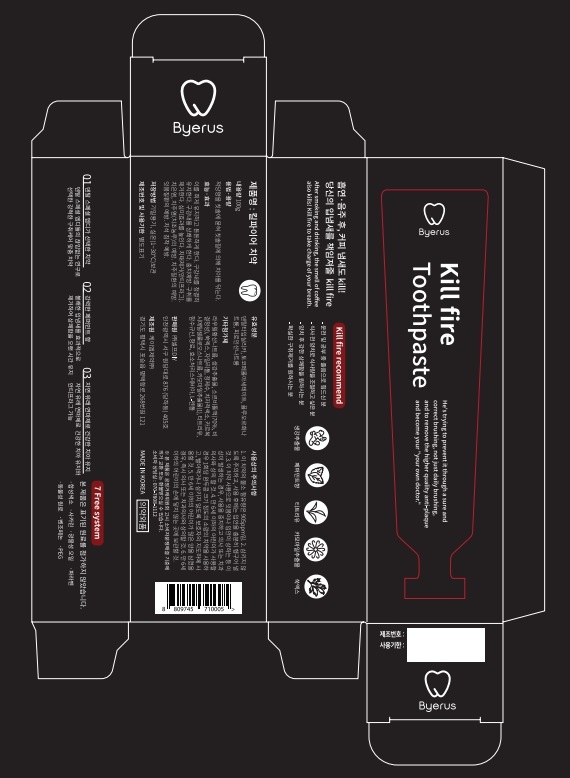 DRUG LABEL: Kill fireToothpaste
NDC: 24765-133 | Form: PASTE
Manufacturer: Pharmacal-International. Co., Ltd.
Category: otc | Type: HUMAN OTC DRUG LABEL
Date: 20241025

ACTIVE INGREDIENTS: SODIUM FLUORIDE 0.02 g/100 g
INACTIVE INGREDIENTS: SODIUM PYROPHOSPHATE; .ALPHA.-TOCOPHEROL ACETATE; SORBITOL; XYLITOL; HYDRATED SILICA; SODIUM LAURYL SULFATE; MENTHOL, UNSPECIFIED FORM; MATRICARIA CHAMOMILLA WHOLE; GINGER; TEA TREE OIL; WATER

Active ingredient

Sodium Fluoride 0.02%

Purpose

- Anticavity Toothpaste

Use

- Aids in the prevention of dental cavities

Directions

- Apply appropriate amount on a toothbrush and brush teeth.

Warnings

- Be careful not to swallow. Rinse mouth thoroughly after use.
- If pain occurs when using this product, stop using and consult your dentist.
- For children under 6 years of age, use a pea size amount of toothpaste as recommended by the KFDA. Use under the guidance of a guardian.
- If a child under 6 years old swallows a large amount, consult a physician or dentist immediately.
- Keep out of the reach of children under 6 years old.

Inactive ingredients

Silica,Sorbitol, Tetrasodium Pyrophosphate, Tocopheryl Acetate,
Xylitol, Glucosyl Stevioside, Hydrated Silica, Cellulose Gum, Sodium lauryl Sulfate, Menthol,
Chamomilla Recutita (Matricaria) Extract, Artemisia Princeps Extract, Zingiber Officinale (Ginger) Root Extract,
Melaleuca Alternifolia (Tea Tree) Leaf Oil, Flavor, Gardenia Red, Water

Effect- Efficacy

- Whitens teeth while fighting germs
- Long-lasting freshness and clean mouth feel
- Protects against cavities and bad breath
- Natural brightness of your teeth shines
- Anti plaque
- Helps prevent plaque, gingivitis cavities and gum disease